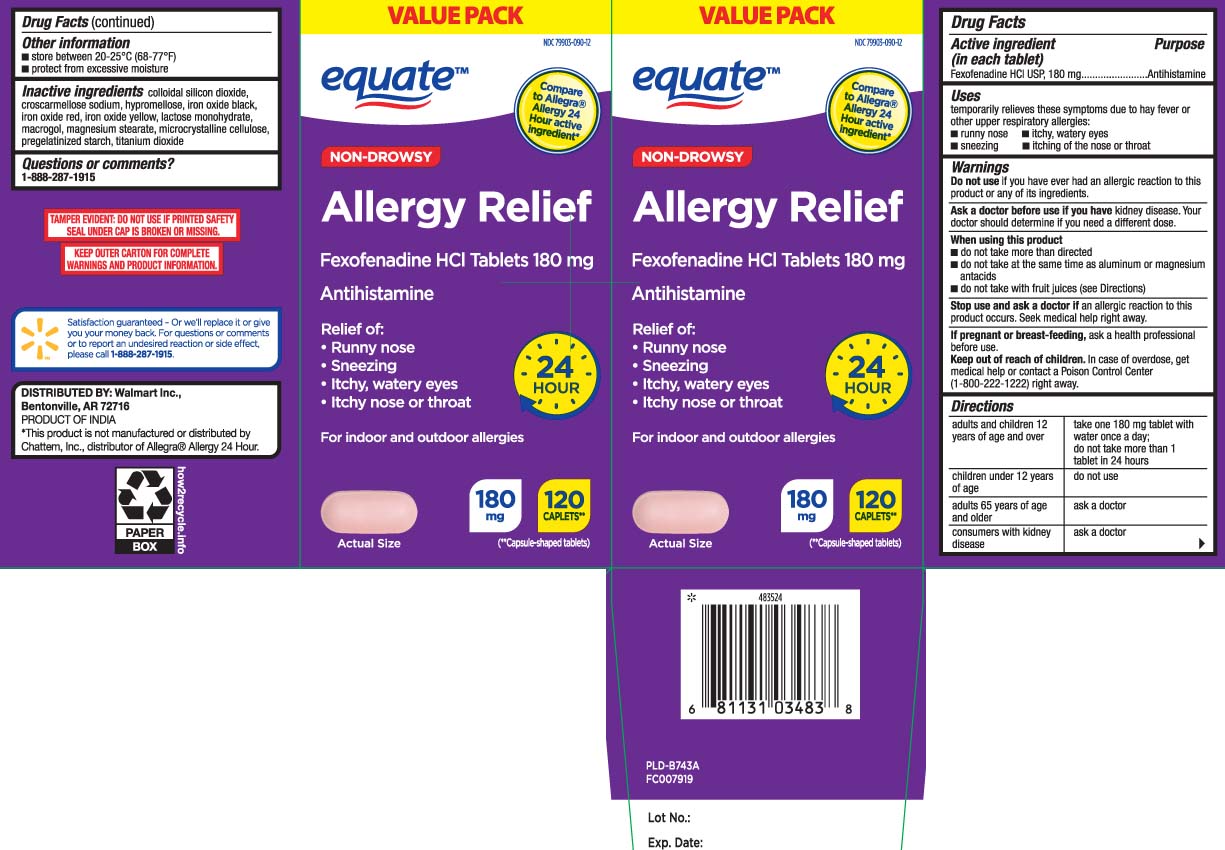 DRUG LABEL: Allergy Relief
NDC: 79903-090 | Form: TABLET
Manufacturer: WALMART INC. (see also Equate)
Category: otc | Type: HUMAN OTC DRUG LABEL
Date: 20230209

ACTIVE INGREDIENTS: FEXOFENADINE HYDROCHLORIDE 180 mg/1 1
INACTIVE INGREDIENTS: SILICON DIOXIDE; CROSCARMELLOSE SODIUM; HYPROMELLOSES; FERRIC OXIDE RED; FERRIC OXIDE YELLOW; LACTOSE MONOHYDRATE; POLYETHYLENE GLYCOL, UNSPECIFIED; TITANIUM DIOXIDE; STARCH, CORN; FERROSOFERRIC OXIDE; MAGNESIUM STEARATE; CELLULOSE, MICROCRYSTALLINE

DRUG FACTS

Active ingredient (in each tablet)

Fexofenadine HCl USP, 180 mg

Purpose

Antihistamine

Uses

temporarily relieves these symptoms due to hay fever or other upper respiratory allergies:

- runny nose
- itchy, watery eyes
- sneezing
- itching of the nose or throat

Warnings

Do not use

if you have ever had an allergic reaction to this product or any of its ingredients.

Ask a doctor before use if you have

kidney disease. Your doctor should determine if you need a different dose.

When using this product

- do not take more than directed
- do not take at the same time as aluminum or magnesium antacids
- do not take with fruit juices (see Directions)

Stop use and ask a doctor if

an allergic reaction to this product occurs. Seek medical help right away.

If pregnant or breast-feeding,

ask a health professional before use.

Keep out of reach of children.

In case of overdose, get medical help or contact a Poison Control Center (1-800-222-1222) right away.

Directions

adults and children 12 years of age and over | take one 180 mg tablet with water once a day; do not take more than 1 tablet in 24 hours
children under 12 years of age | do not use
adults 65 years of age and older | ask a doctor
consumers with kidney disease | ask a doctor

Other information

- store between 20-25ºC (68-77ºF)
- protect from excessive moisture

Inactive ingredients

colloidal silicon dioxide, corn starch, croscarmellose sodium, hypromellose, iron oxide black, iron oxide red, iron oxide yellow, lactose monohydrate, polyethylene glycol, magnesium stearate, microcrystalline cellulose, pregelatinized starch, titanium dioxide

Questions or comments?

1-888-287-1915

Principal Display Panel

Compare to Allegra® Allergy 24 hour active ingredient*

NON-DROWSY

Allergy Relief

Fexofenadine HCl Tablets 180 mg

Antihistamine

Relief of:

- Runny Nose
- Sneezing
- Itchy, Watery Eyes
- Itchy Nose or Throat

For indoor and outdoor allergies

CAPLETS**

(**capsules-shaped tablets)

*This product is not manufactured or distributed by Chattem Inc., distributor of Allegra® Allergy 24 hour

TAMPER EVIDENT: DO NOT USE IF PRINTED SAFETY SEAL UNDER CAP IS BROKEN OR MISSING.

KEEP OUTER CARTON FOR COMPLETE WARNINGS AND PRODUCT INFORMATION.

DISTRIBUTED BY: Walmart Inc.,

Bentonville, AR 72716

Product Label

EQUATE Allergy Relief